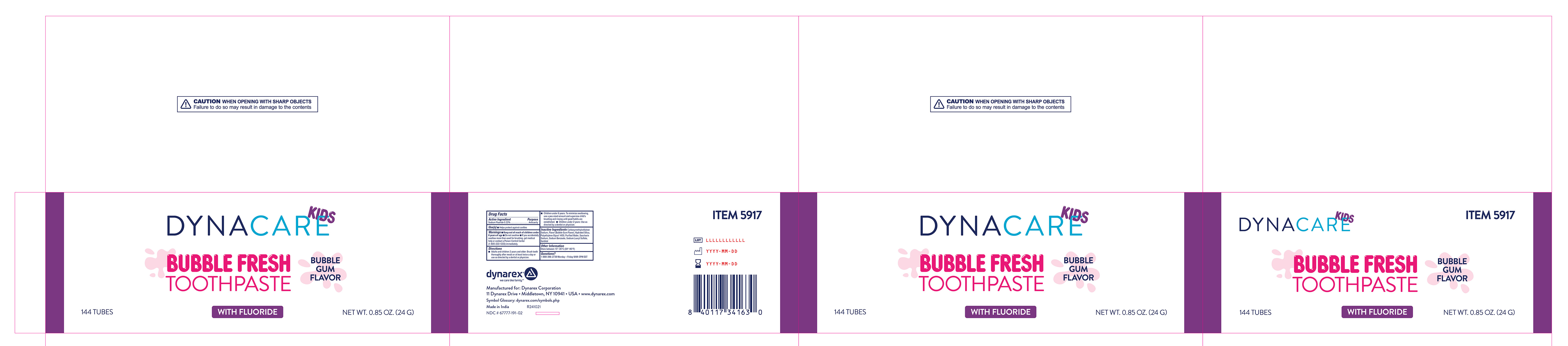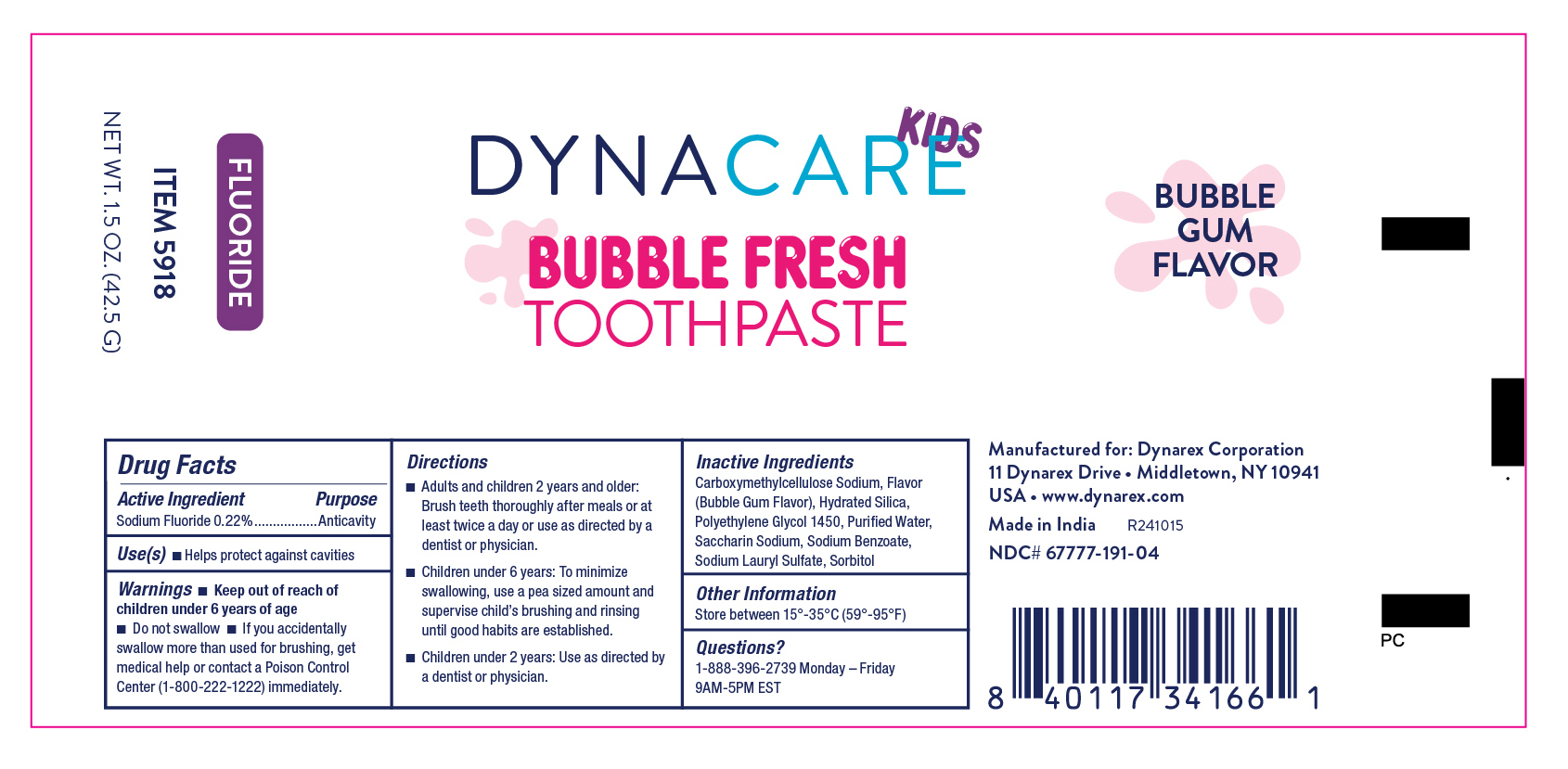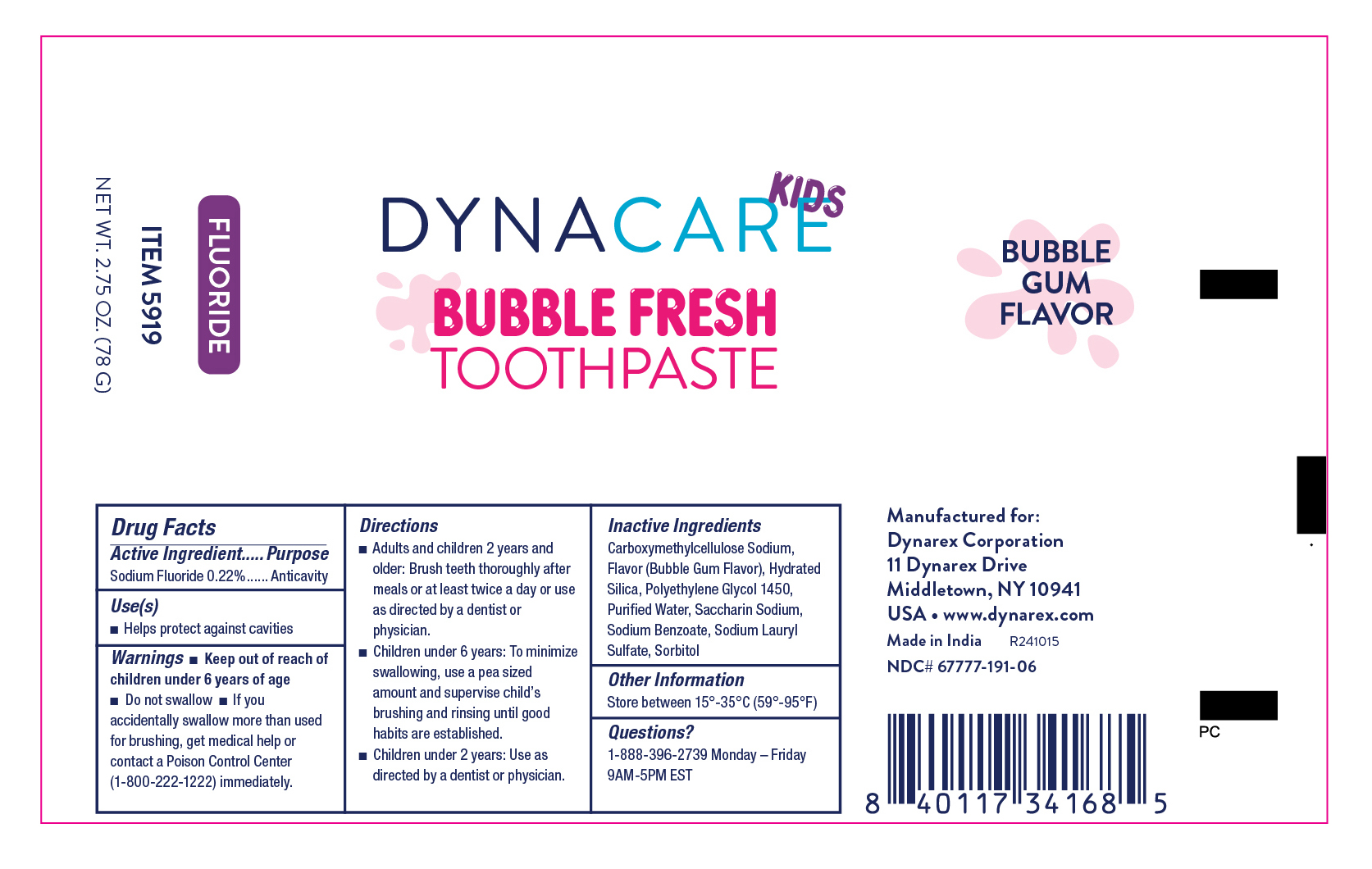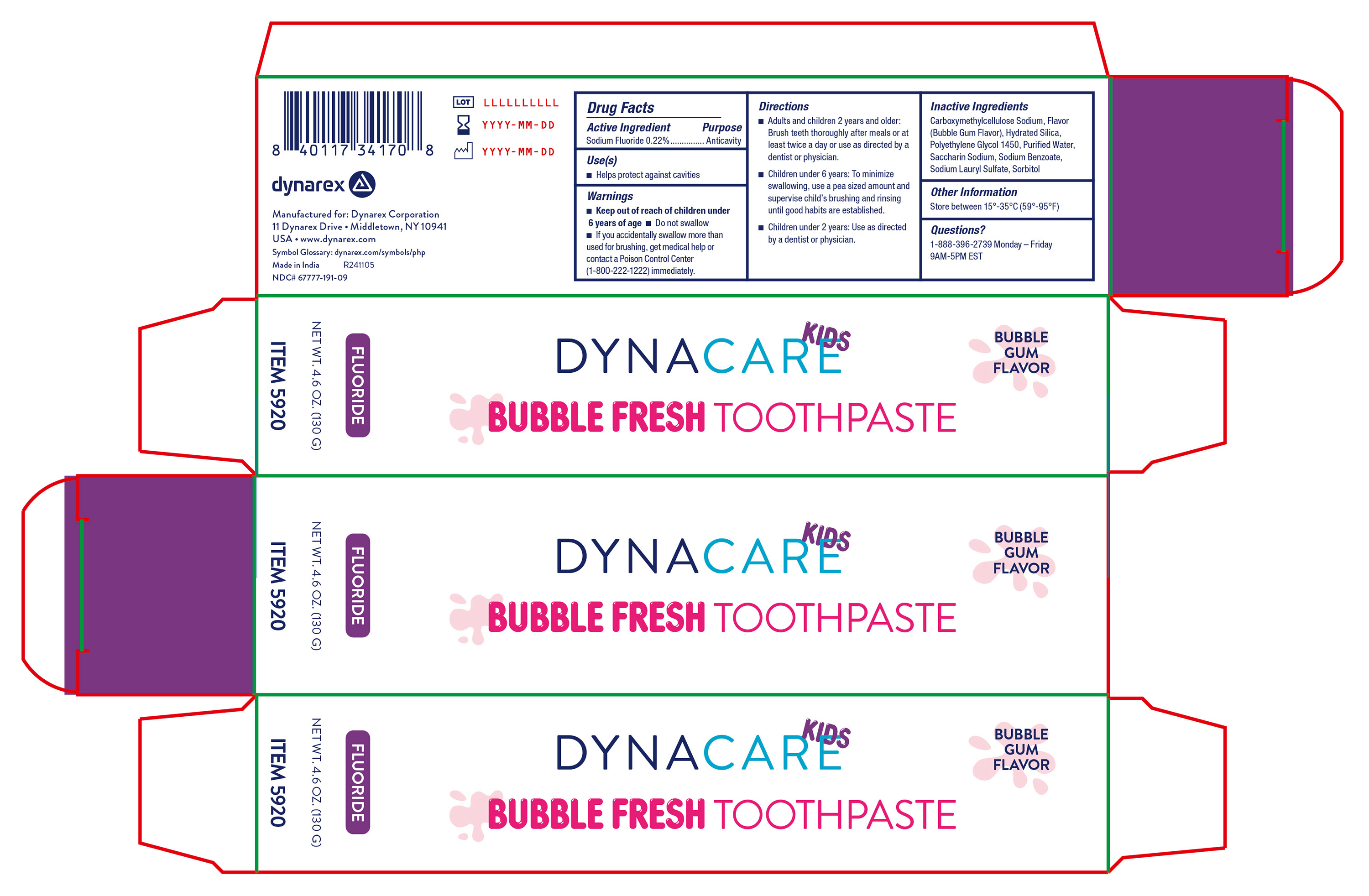 DRUG LABEL: Bubble Fresh Toothpaste, with Fluoride
NDC: 67777-191 | Form: PASTE
Manufacturer: Dynarex Corporation
Category: otc | Type: HUMAN OTC DRUG LABEL
Date: 20241226

ACTIVE INGREDIENTS: SODIUM FLUORIDE 220 mg/1 g
INACTIVE INGREDIENTS: HYDRATED SILICA; POLYETHYLENE GLYCOL 1450; SORBITOL; SACCHARIN SODIUM; SODIUM LAURYL SULFATE; SODIUM BENZOATE; WATER; CARBOXYMETHYLCELLULOSE SODIUM

5917 Bubble Fresh Toothpaste.85 oz.
5918 Bubble Fresh Toothpaste 1.5 oz.
5919 Bubble Fresh Toothpaste 2.75 oz.
5920 Bubble Fresh Toothpaste 4.6 oz.

Active Ingredient

Sodium Fluoride 0.22%

Purpose

Anticavity

Use(s)

Helps protect against cavities

Warnings

Do Not Swallow

Keep our to reach of children under 6 years of age

If you accidentally swallow more than used for brushing, get medical help or contact a Poison Control Center (1-800-222-1222) immediately.

Directions

• Adults and children 2 years of age and older: Brush teeth thoroughly after meals or at least twice a day or use as directed by a dentist or physician.

• Children under 6 years: To minimize swallowing, use a pea size amount and supervise child's brushing and rinsing until good habits are established.

• Children under 2 years: Use as directed by a dentist or physician

Inactive Ingredients

Carboxymethylcellulose Sodium, Flavor (Bubble Gum Flavor), Hydrated Silica Polyethylene Glycol 1450, Purified Water, Saccharin Sodium, Sodium Benzoate, Sodium Lauryl Sulfate, Sorbitol

Other Information

Store between 15º - 35ºC (59º - 95ºF)

Questions?

1-888-396-2739 Monday - Friday 9AM - 5PM EST

Label

5917 Bubble Fresh Toothpaste with Fluoride

Label

5918 Bubble Fresh Toothpaste with Fluoride

Label

5919 Bubble Fresh Toothpaste with Fluoride

Label

5920 Bubble Fresh Toothpaste with Fluoride